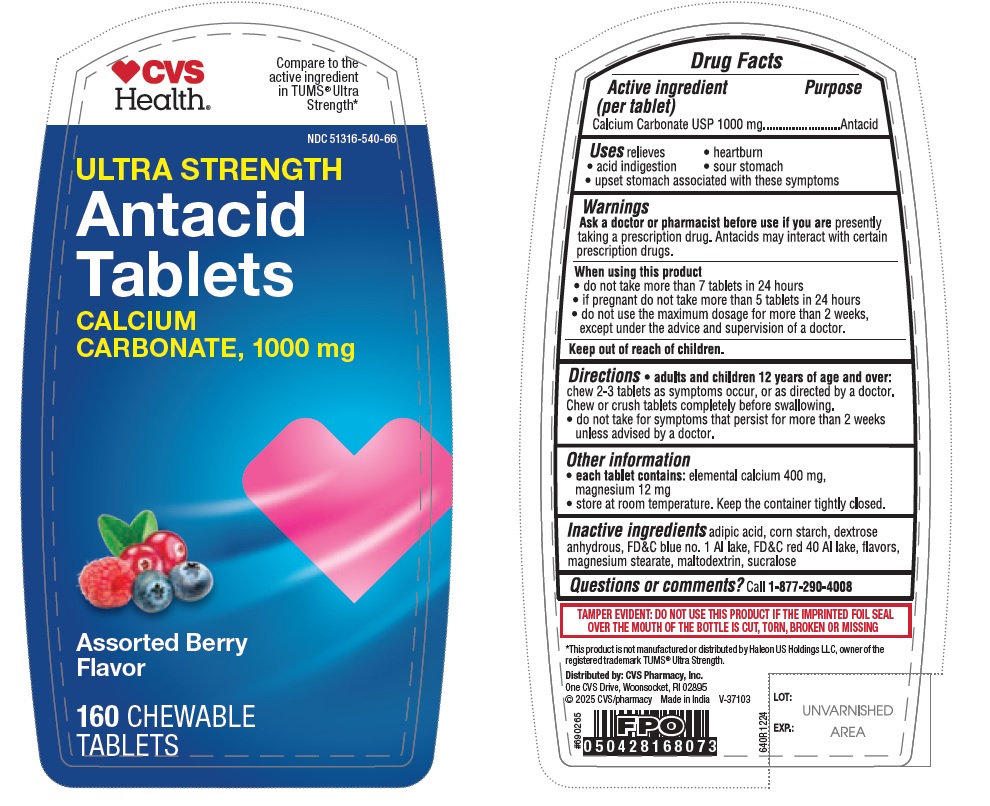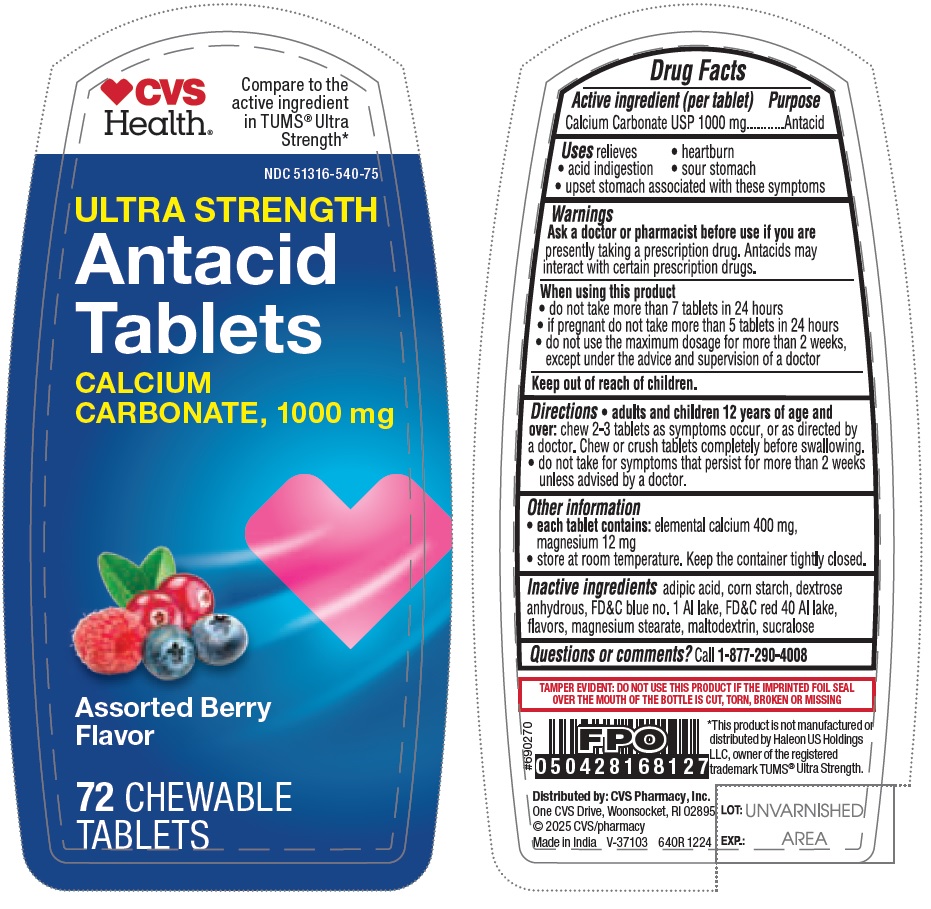 DRUG LABEL: Maximum Strength Calcium Carbonate 1000mg
NDC: 51316-540 | Form: TABLET, CHEWABLE
Manufacturer: CVS HEALTH CORP
Category: otc | Type: HUMAN OTC DRUG LABEL
Date: 20250410

ACTIVE INGREDIENTS: CALCIUM CARBONATE 1000 mg/1 1
INACTIVE INGREDIENTS: MAGNESIUM STEARATE; SUCRALOSE; ADIPIC ACID; FD&C BLUE NO. 1 ALUMINUM LAKE; STARCH, CORN; FD&C RED NO. 40 ALUMINUM LAKE; ANHYDROUS DEXTROSE; MALTODEXTRIN

640R CVS Calcium Carbonate 1000 mg Chewable Tablets - Assorted Berry

Drug Facts

Active ingredient (per tablet)

Calcium Carbonate USP 1000 mg

Purpose

Antacid

INDICATIONS AND USAGE

Uses relieves

- heartburn
- acid indigestion
- sour stomach
- upset stomach associated with these symptoms

Warnings

Ask a doctor or pharmacist before use if you are presently taking a prescription drug. Antacids may interact with certain prescription drugs.

When using this product

- do not take more than 7 tablets in 24 hours
- if pregnant do not take more than 5 tablets in 24 hours
- do not use the maximum dosage for more than 2 weeks, except under the advice and supervision of a doctor

Keep out of reach of children.

Directions

- adults and children 12 years of age and over: chew 2-3 tablets as symptoms occur, or as directed by a doctor. Chew or crush tablets completely before swallowing.
- do not take for symptoms that persist for more than 2 weeks unless advised by a doctor.

Other information

- each tablet contains: elemental calcium 400 mg, magnesium 12 mg
- store at room temperature. Keep the container tightly closed.

INACTIVE INGREDIENT

Inactive ingredients adipic acid, corn starch, dextrose anhydrous, FD&C blue no. 1 Al lake, FD&C red 40 Al lake, flavors, magnesium stearate, maltodextrin, sucralose

Questions or comments? Call 1-877-290-4008